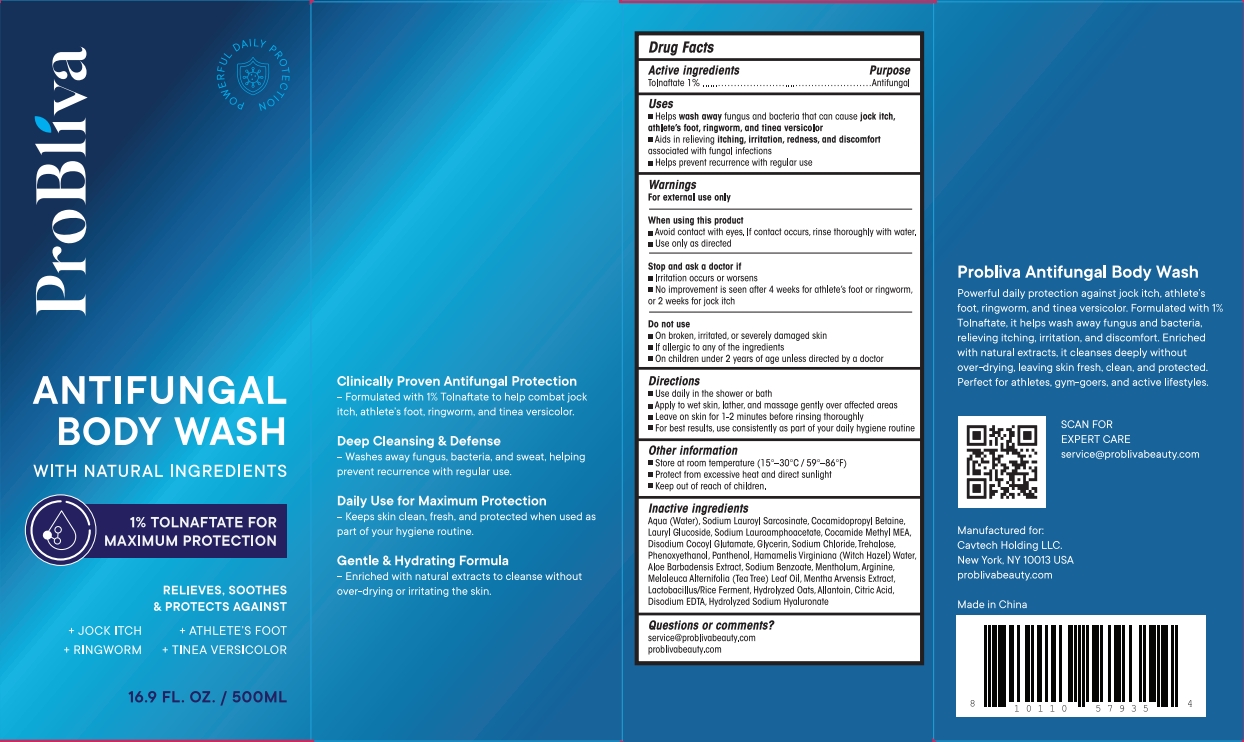 DRUG LABEL: Antifungal Boday Wash
NDC: 85464-001 | Form: SOAP
Manufacturer: CAVTECH HOLDING LLC
Category: otc | Type: HUMAN OTC DRUG LABEL
Date: 20250527

ACTIVE INGREDIENTS: TOLNAFTATE 1 mg/100 mL
INACTIVE INGREDIENTS: LAURYL GLUCOSIDE; ALLANTOIN; SODIUM HYALURONATE; TREHALOSE; AQUA; COCAMIDOPROPYL BETAINE; COCAMIDE METHYL MEA; DISODIUM COCOYL GLUTAMATE; PHENOXYETHANOL; SODIUM BENZOATE; MELALEUCA ALTERNIFOLIA (TEA TREE) LEAF OIL; CITRIC ACID; ALOE BARBADENSIS LEAF; LACTOBACILLUS; MENTHA ARVENSIS LEAF OIL; SODIUM LAUROAMPHOACETATE; SODIUM LAUROYL SARCOSINATE; GLYCERIN; SODIUM CHLORIDE; PANTHENOL; HAMAMELIS VIRGINIANA (WITCH HAZEL) LEAF WATER; ARGININE; CALCIUM DISODIUM EDTA; AVENA SATIVA (OAT) STARCH; SODIUM COCOYL GLYCINATE; MENTHOL

Probliva Antifungal Boday Wash

ACTIVE INGREDIENT

Tolnaftate 1%

PURPOSE

Antifungal

INDICATIONS AND USAGE

- Helps wash away fungus and bacteria that can cause jock itch, athlete's foot, ringworm, andtinea versicolor
- Aids in relieving itching, irritation, redness, and discomfort associated with fungal infections
- Helps prevent recurrence with regular use

WARNINGS

For external use only

WHEN USING

- Avoid contact with eyes. lf contact occurs, rinse thoroughly with water.
- Use only as directed

STOP USE

- lrritation occurs or worsens
- No improvement is seen after 4 weeks for athlete's foot or ringworm, or 2 weeks for jock itch

DO NOT USE

- On broken, irritated, or severely damaged skin
- If allergic to any ingredients
- On children under 2 years of age unless directed by a doctor

keep out of reach of children

DOSAGE AND ADMINISTRATION

- Use daily in the shower or bath
- Apply to wet skin, lather, and massage gentlyover affected areas
- Leave on skin for 1-2 minutes before rinsing thoroughly
- For bestresults,use consistently as part of your daily hygiene routine

OTHER SAFETY INFORMATION

- Store at room temperature(15°-30°C/59°-86°F)
- Protect fromexcessive heat and direct sunlight

INACTIVE INGREDIENT

Aqua (Water), Sodium Lauroyl Sarcosinate,Cocamidopropy! Betaine, Lauryl Glucoside, Sodium Lauroamphoacetate, Cocamide Methy! MEA, Disodium Cocoyl Glutamate, Glycerin, Sodium Chloride,Trehalose, Phenoxyetha-nol, Panthenol, Hamamelis Virginiana (Witch Hazel) Water,Aloe Barbadensis Extract, Sodium Benzoate,Mentholum,Arginine, Melaleuca Alterifolia (Tea Tree) Leaf Oil,Mentha Arvensis Extract,Lactobacillus/RiceFerment, Hydrolyzed Oats, Allantoin, Citric Acid, Disodium EDTA, Hydrolyzed Sodium Hyaluronate

QUESTIONS

service@problivabeauty.com
problivabeauty.com